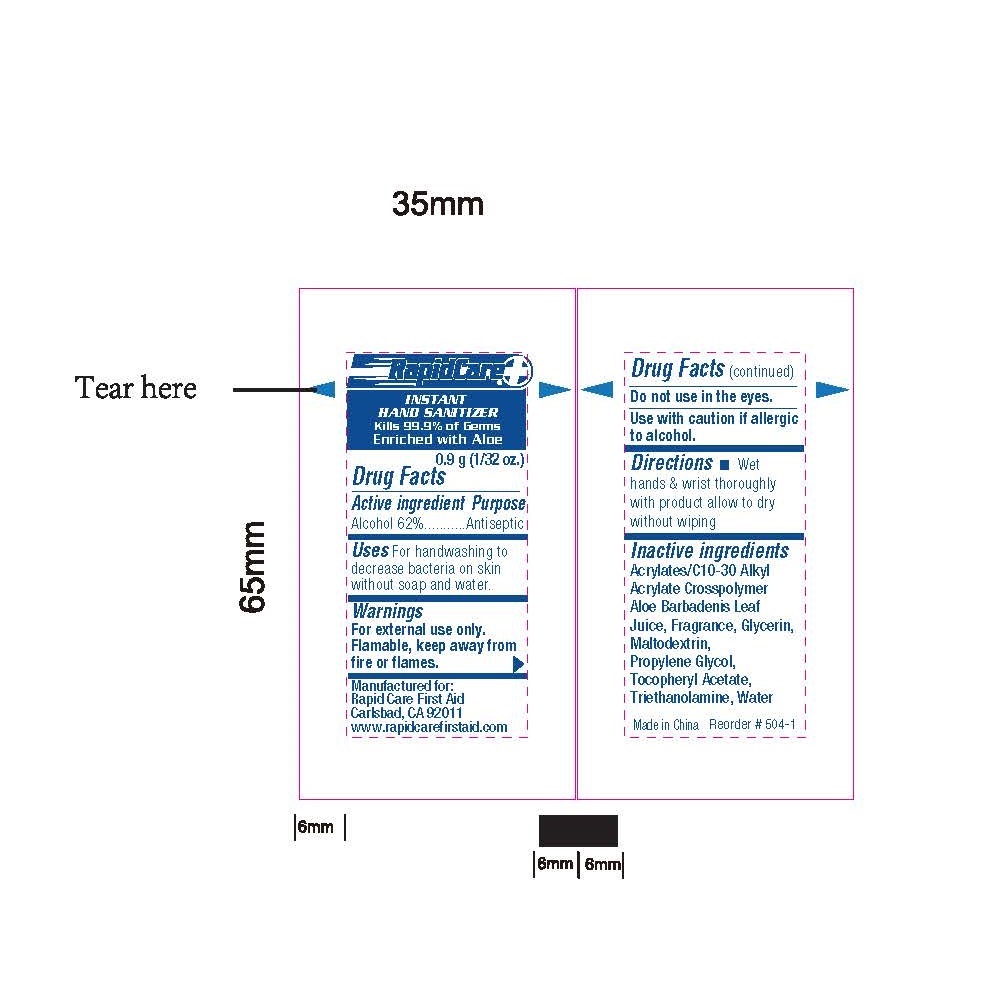 DRUG LABEL: Hand Sanitizer
NDC: 73659-007 | Form: SWAB
Manufacturer: Rapid Care, Inc
Category: otc | Type: HUMAN OTC DRUG LABEL
Date: 20201101

ACTIVE INGREDIENTS: ALCOHOL 0.62 mL/1 1
INACTIVE INGREDIENTS: WATER; GLYCERIN; CARBOMER INTERPOLYMER TYPE A (55000 CPS); MALTODEXTRIN; ALOE; ALPHA-TOCOPHEROL ACETATE; PROPANEDIOL

RapidCare - Hand Sanitizer - 1pc

Active Ingredients

Alcohol 62%

Purpose

Antiseptic

Uses

For handwashing to decrease bacteria on skin without soap and water

Warnings

For external use only.

Flammable, keep away from fire or flames.

Do not use in the eyes. If this happens, rinse thoroughly with water.

Use with caution if allergic to alcohol.

Do not use

in the eyes. If this happens, rince thoroughly with water

Keep out of reach of children.

If ingested get medical help or contact a Poison Control Center right away

Directions

- Wet hands & wrists thoroughly with product and allow to dry without wiping

Inactive ingredient

Acrylates/C10-30 Alkyl, Acrylate, Crosspolymer, Aloe Barbadenis Leaf Juice, Fragrance, Glycerin, Maltodextrin, Proplen Glycol, Tocpheryl Acetate, Triethanolamine, Water